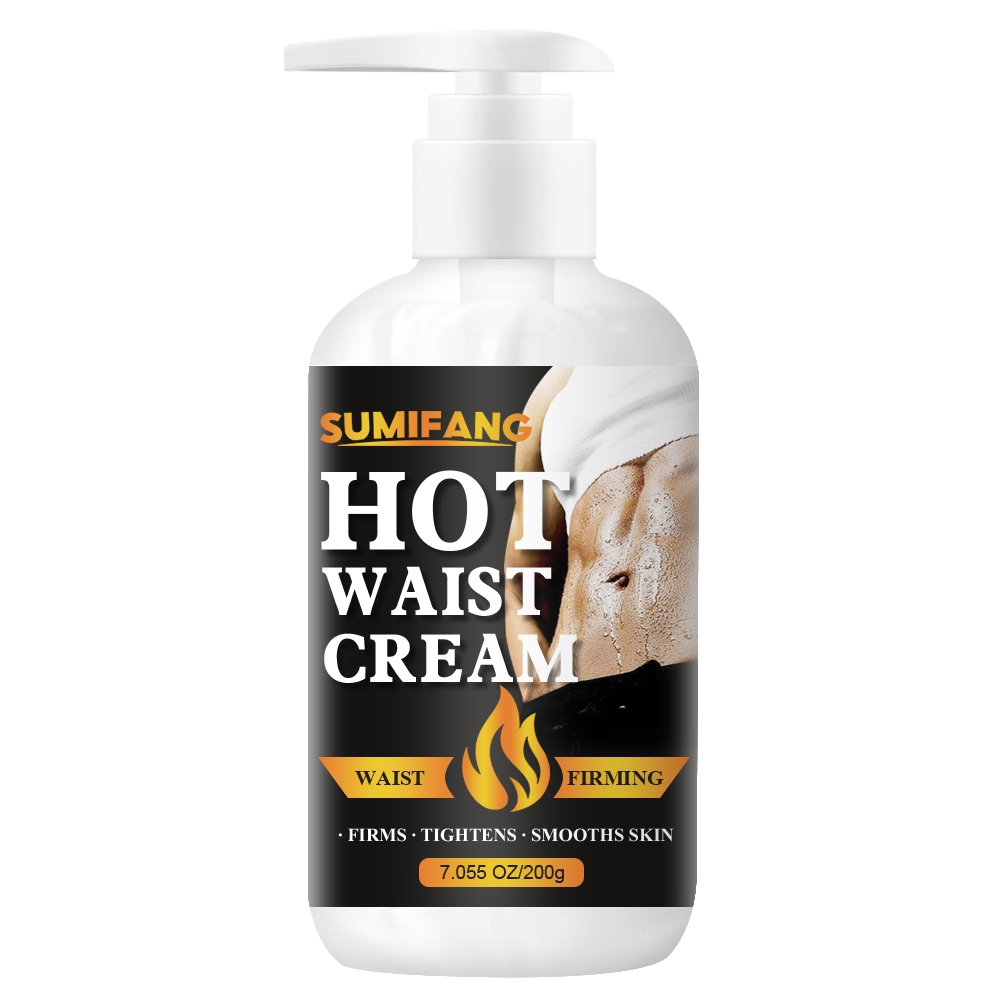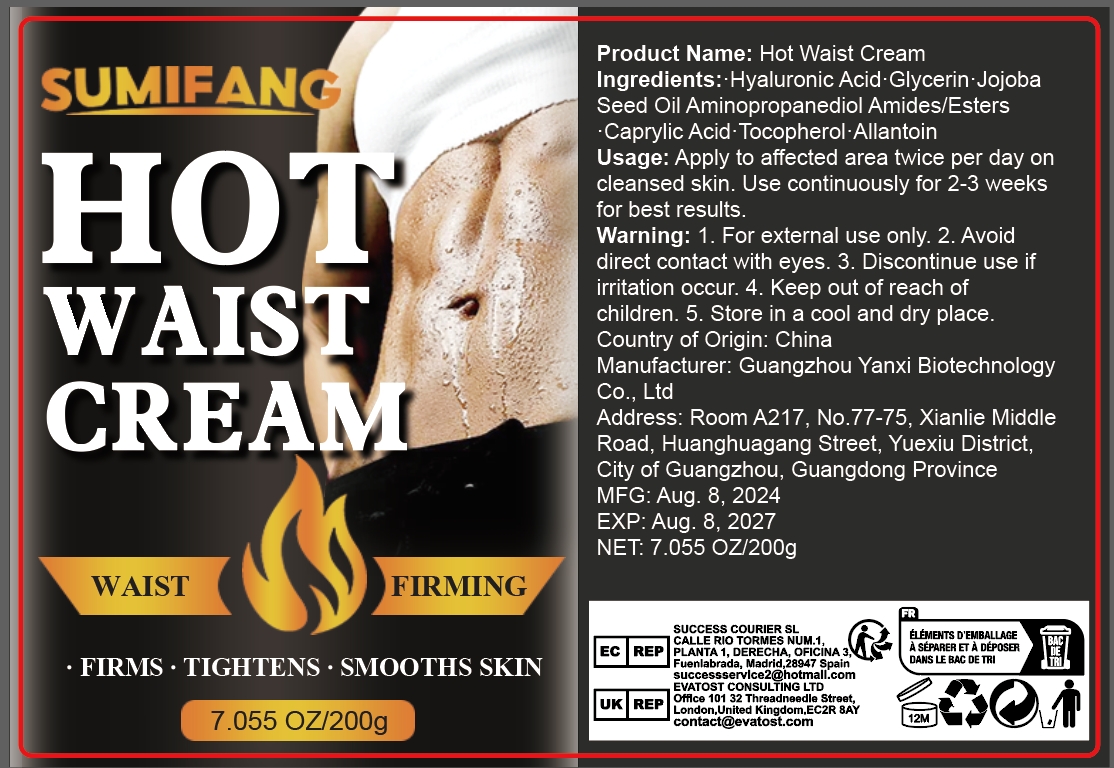 DRUG LABEL: HOT WAISTCREAM
NDC: 84025-131 | Form: CREAM
Manufacturer: Guangzhou Yanxi Biotechnology Co.. Ltd
Category: otc | Type: HUMAN OTC DRUG LABEL
Date: 20240812

ACTIVE INGREDIENTS: GLYCERIN 5 mg/200 g; CAPRYLIC ACID 3 mg/200 g
INACTIVE INGREDIENTS: WATER

DOSAGE AND ADMINISTRATION

Cream for waist massage

WARNINGS

Keep out of children

INACTIVE INGREDIENT

Aqua

INDICATIONS AND USAGE

Apply to affected area twice per day on cleansed skin.Use continuously for 2-3 weeks for best results.

Keep out of children

PURPOSE

For firming and smoothing abdominal skin